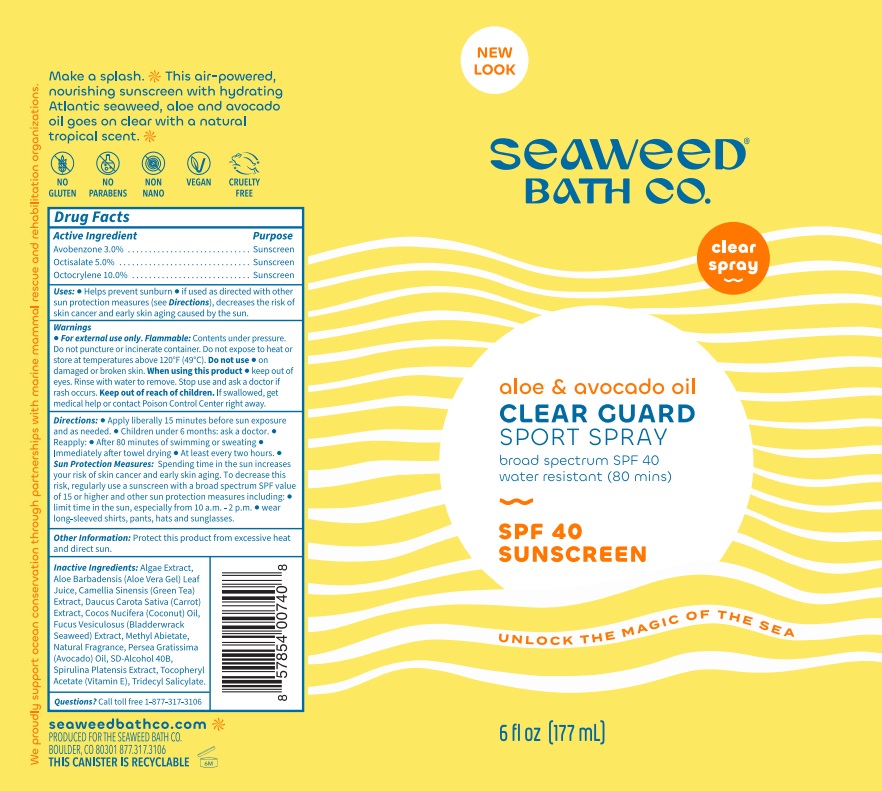 DRUG LABEL: SEAWEED BATH CO SPF 40 SPORT
NDC: 81159-132 | Form: SPRAY
Manufacturer: The Seaweed Bath Co.
Category: otc | Type: HUMAN OTC DRUG LABEL
Date: 20240626

ACTIVE INGREDIENTS: AVOBENZONE 30 mg/1 mL; OCTISALATE 50 mg/1 mL; OCTOCRYLENE 100 mg/1 mL
INACTIVE INGREDIENTS: TRIDECYL SALICYLATE; ALOE VERA LEAF; GREEN TEA LEAF; CARROT; COCONUT OIL; FUCUS VESICULOSUS; METHYL ABIETATE; AVOCADO OIL; ARTHROSPIRA PLATENSIS; .ALPHA.-TOCOPHEROL ACETATE

SEAWEED BATH CO. SPF-40 SPORT SPRAY

Active Ingredient

Avobenzone 3.0%

Octisalate 5.0%

Octocrylene 10.0%

Purpose

Sunscreen

Uses:

• Helps prevent sunburn. • Higher SPF gives more sunburn protection. • Retains SPF after 80 minutes of swimming or sweating.

Warnings:

Contents under pressure. Do not puncture or incinerate container. Do not expose to heat or store at temperatures above 120°F (49°C). For external use only. Flammable:

Do not use

on damaged or broken skin.

When using this product

- keep out of eyes. Rinse with water to remove.

Stop use and ask a doctor

- if rash occurs.

Keep out of reach of children.

• If swallowed, get medical help or contact a Poison Control Center right away.

Directions:

• Apply liberally 15 minutes before sun exposure and as needed. • Children under 6 months: ask a doctor. • Reapply: • After 80 minutes of swimming or sweating • Immediately after towel drying • A t least every two hours. • Sun Protection Measures: Spending time in the sun increases your risk of skin cancer and early skin aging. To decrease this risk, regularly use a sunscreen with a broad spectrum SPF of 15 or higher and other sun protection measures including: • Limit time in the sun, especially from 10 a.m. – 2 p.m. • Wear long-sleeve shirts, pants, hats and sunglasses.

Inactive Ingredients:

Algae Ex tract, Aloe Barbadensis Leaf (Aloe Vera Gel) Juic e, Camell ia Si nensis (Green Tea) E xtr act, Daucus Ca rota S ativa (Car rot) Extrac t, Cocos Nucifer a (Coconut) Oil, Fucus Vesiculosus (Bladderwrack Seaweed) Extract, Methyl Abietate, Natural Fragrance, Persea Gratissima (Avocado) Oil, SD -Alcohol 40B, Spirulina Platensis Extract, Tocopheryl Acetate (Vitamin E), Tridecyl Salicylate.

Other Information:

Protect this product from excessive heat and direct sun.

Questions?

Call toll free 1-877-317-3106